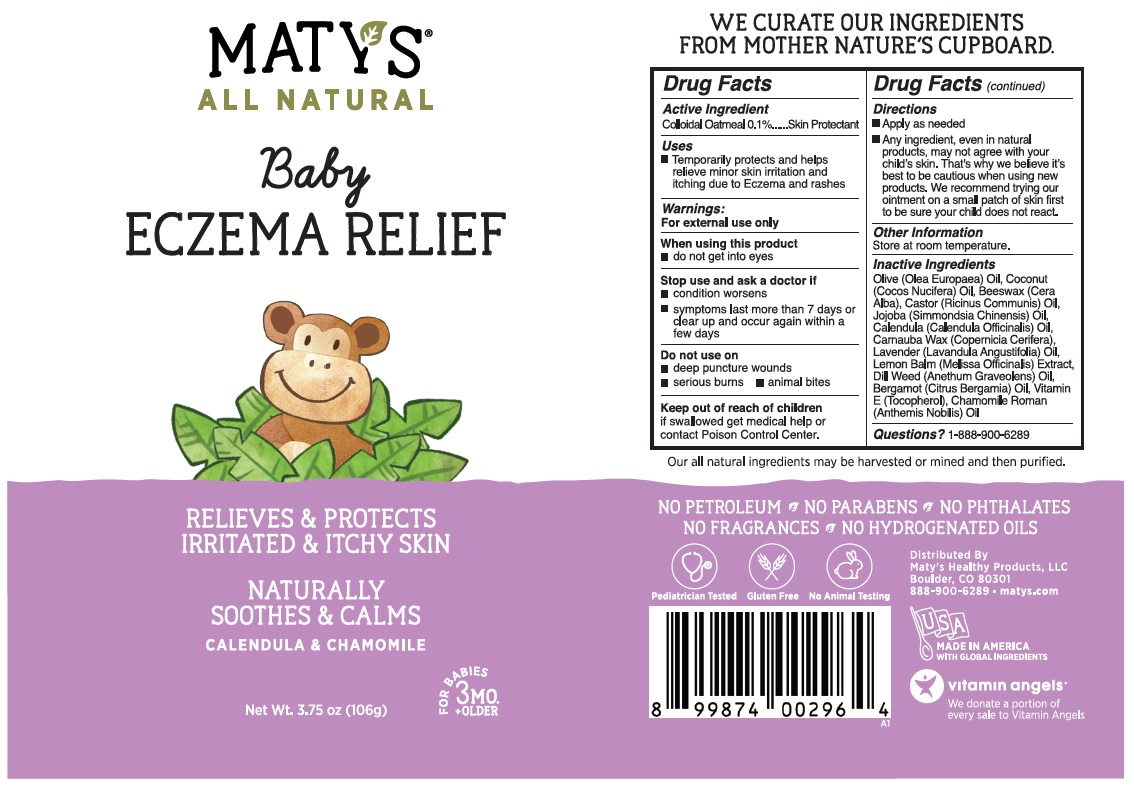 DRUG LABEL: MATYS Baby ECZEMA RELIEF
NDC: 72827-103 | Form: OINTMENT
Manufacturer: Matys Healthy Products LLC
Category: otc | Type: HUMAN OTC DRUG LABEL
Date: 20250129

ACTIVE INGREDIENTS: OATMEAL 0.1 g/100 g
INACTIVE INGREDIENTS: OLIVE OIL; COCONUT OIL; YELLOW WAX; CASTOR OIL; JOJOBA OIL; CALENDULA OFFICINALIS FLOWER; CARNAUBA WAX; LAVENDER OIL; MELISSA OFFICINALIS LEAF; DILLWEED OIL; BERGAMOT OIL; TOCOPHEROL; CHAMAEMELUM NOBILE FLOWER OIL

MATY'S® Baby ECZEMA RELIEF

Active Ingredient

Colloidal Oatmeal 0.1%

Purpose

Skin Protectant

Uses

• Temporarily protects and helps relieve minor skin irritation and itching due to Eczema and rashes

Warnings:

For external use only

When using this product
• do not get into eyes

Stop use and ask a doctor if
• condition worsens
• symptoms last more than 7 days or clear up and occur again within a few days

Do not use on
• deep puncture wounds
• serious burns • animal bites

Keep out of reach of children
if swallowed get medical help or contact Poison Control Center.

Directions

• Apply as needed

• Any ingredient, even in natural products, may not agree with your child's skin. That's why we believe it's best to be cautious when using new products. We recommend trying our ointment on a small patch of skin first to be sure your child does not react.

Other Information

Store at room temperature.

Inactive Ingredients

Olive (Olea Europaea) Oil, Coconut (Cocos Nucifera) Oil, Beeswax (Cera Alba), Castor (Ricinus Communis) Oil, Jojoba (Simmondsia Chinensis) Oil, Calendula (Calendula Officinalis) Oil, Carnauba Wax (Copernicia Cerifera), Lavender (Lavandula Angustifolia) Oil, Lemon Balm (Melissa Officinalis) Extract, Dill Weed (Anethum Graveolens) Oil, Bergamot (Citrus Bergamia) Oil, Vitamin E (Tocopherol), Chamomile Roman (Anthemis Nobilis) Oil

Questions?

1-888-900-6289

ALL NATURAL

RELIEVES & PROTECTS IRRITATED & ITCHY SKIN

NATURALLY SOOTHES & CALMS

CALENDULA & CHAMOMILE

FOR BABIES 3MO. +OLDER

WE CURATE OUR INGREDIENTS FROM MOTHER NATURE'S CUPBOARD.

Our all natural ingredients may be harvested or mined and then purified.

NO PETROLEUM • NO PARABENS • NO PHTHALATES
NO FRAGRANCES • NO HYDROGENATED OILS

Pediatrician Tested

Gluten Free

No Animal Testing

Distributed By
Maty's Healthy Products, LLC
Boulder, CO 80301
888-900-6289 · matys.com

MADE IN AMERICA
WITH GLOBAL INGREDIENTS

vitamin angels®

We donate a portion of every sale to Vitamin Angels